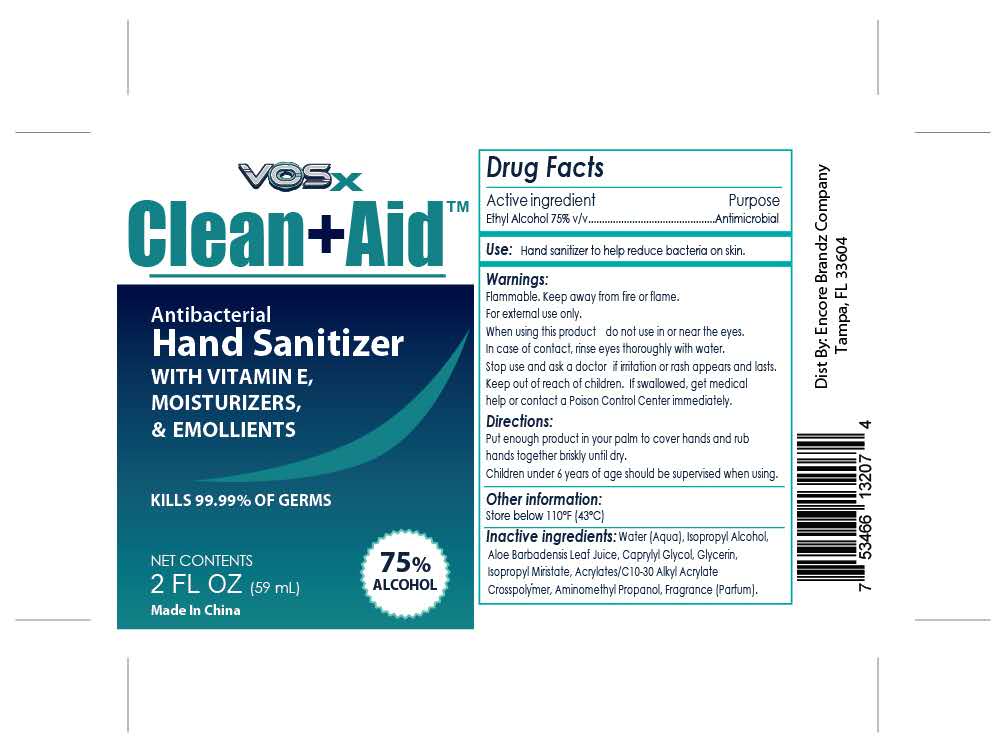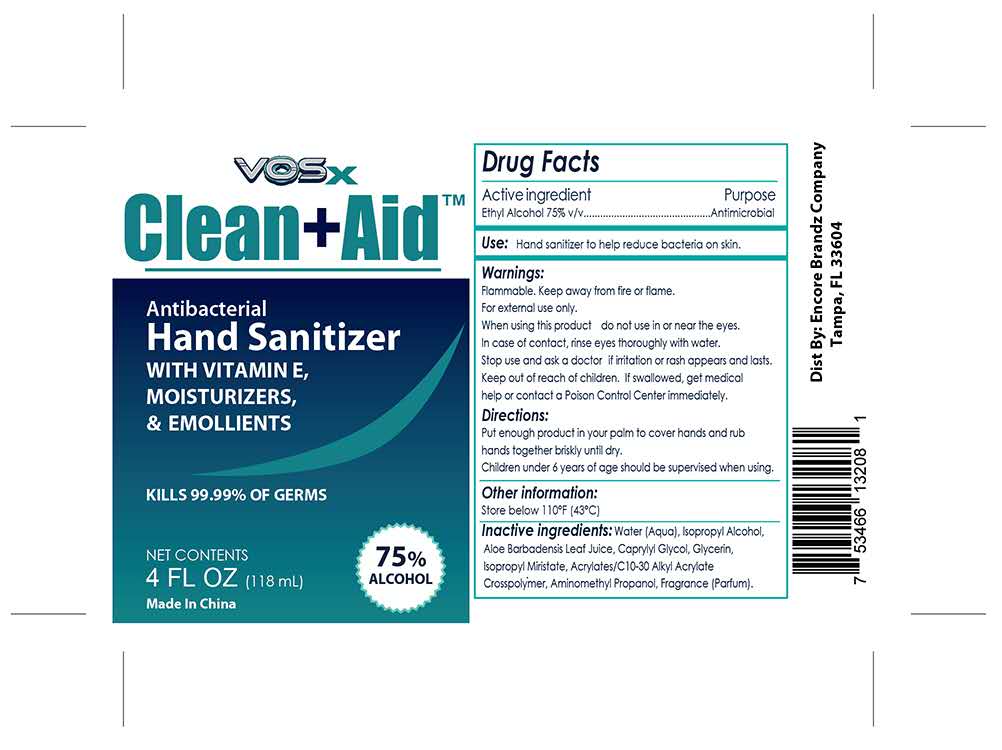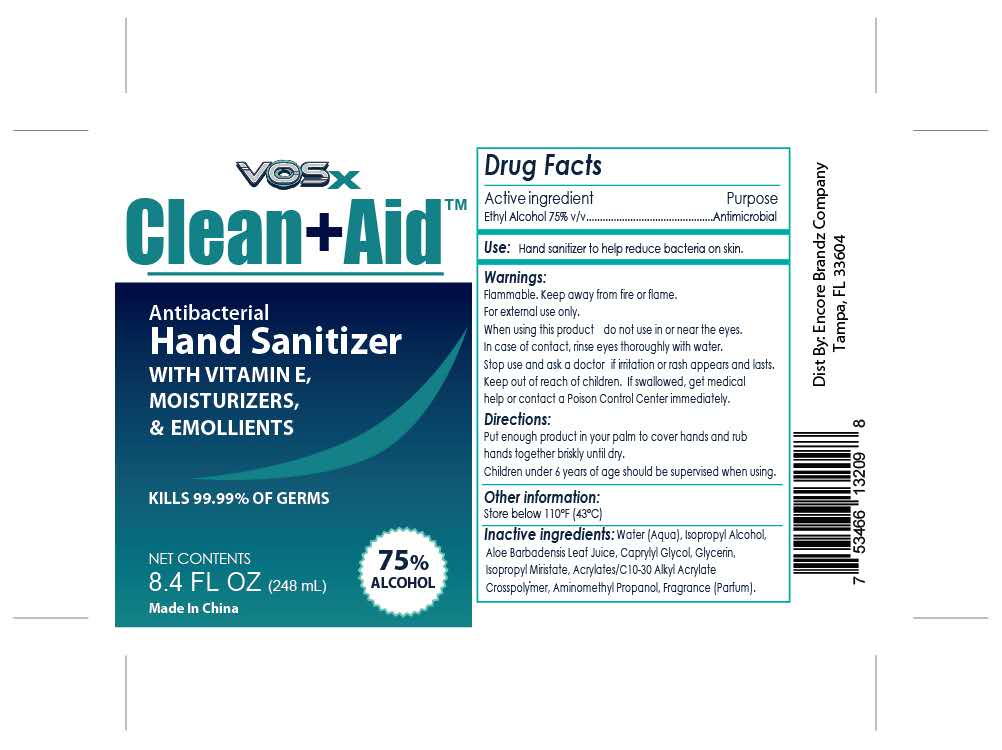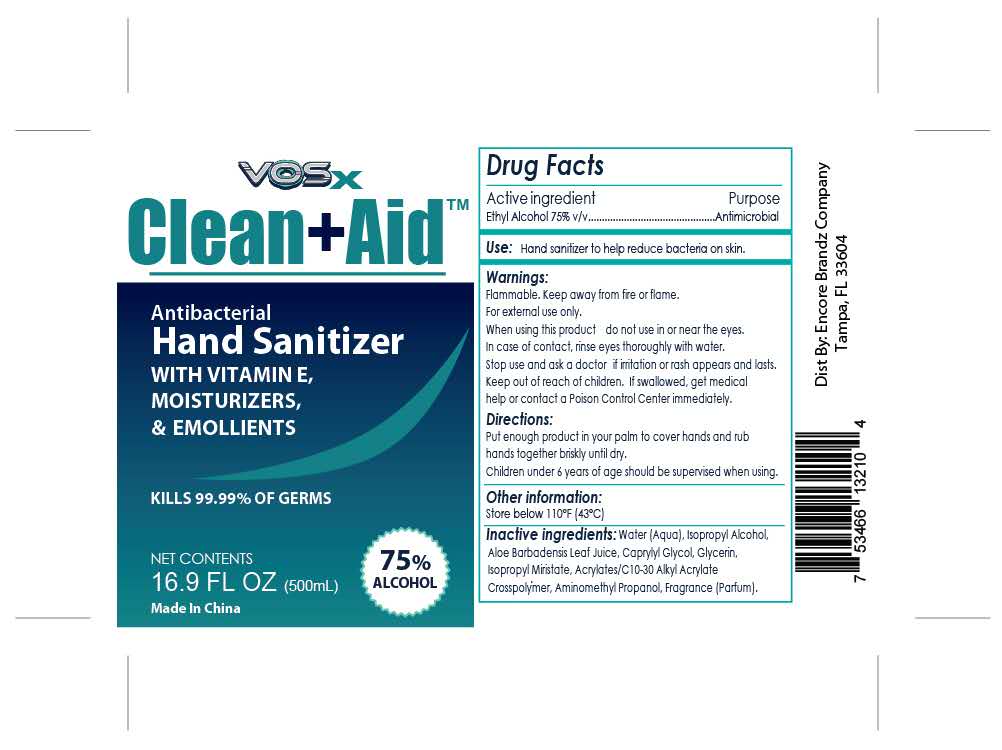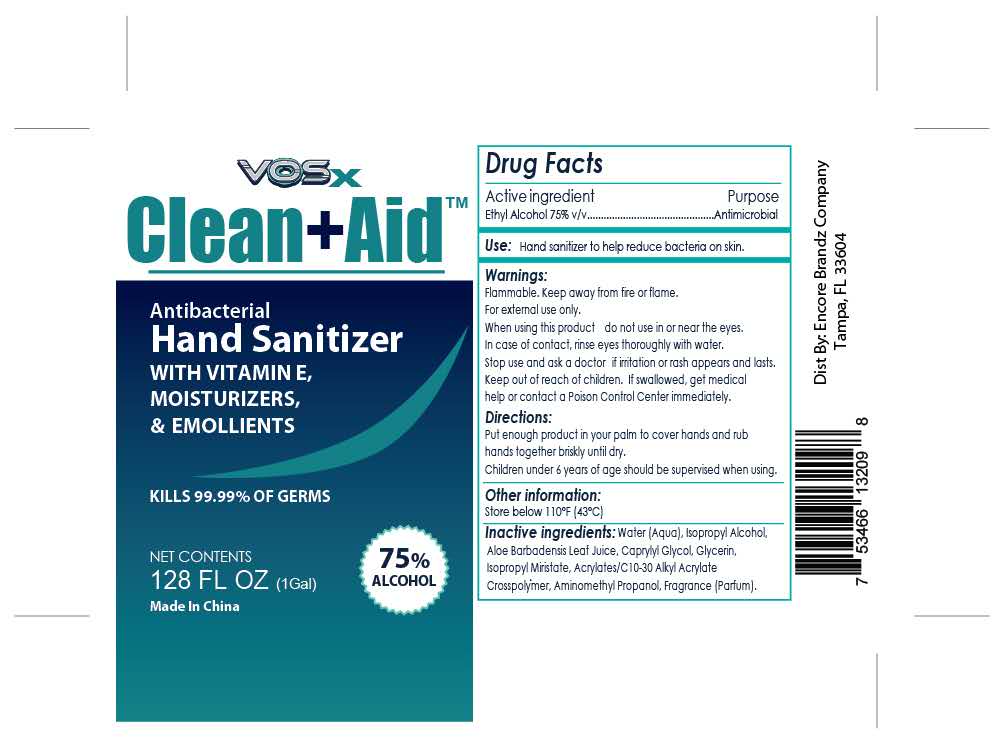 DRUG LABEL: Antibacterial Hand Sanitizer
NDC: 74881-008 | Form: GEL
Manufacturer: Huizhou Baozi Biotechnology Co., Ltd.
Category: otc | Type: HUMAN OTC DRUG LABEL
Date: 20200819

ACTIVE INGREDIENTS: ALCOHOL 75 mL/100 mL
INACTIVE INGREDIENTS: ALOE VERA LEAF; AMINOMETHYLPROPANOL; GLYCERIN; ISOPROPYL MYRISTATE; CARBOMER INTERPOLYMER TYPE A (55000 CPS); CAPRYLYL GLYCOL; WATER; ISOPROPYL ALCOHOL

008 Antibacterial Hand Sanitizer

Active Ingredient

Ethyl Alcohol 75% v/v.

Purpose

Antimicrobial

Uses

Hand sanitizer to help reduce bacteria on skin

Warnings

Flammable. Keep away from fre or fiame
For external use only.

When using this product do not use in or near the eyes

when using this product do not use in or near the eyes
In case of contact, rinse eyes thoroughly with water.

stop use and ask a doctor if imitation or rash appears and lasts.

Keep out of reach of children. If swallowed, get medical help or contact a Poison Control Center right away

Directions

Directions: Place enough product in your palm to thoroughly spread on both hands and rub into the skin until dry

Children under 6 years of age should be supervised when using this product

Other information

Store below 106F(41C).May discolor certain fabnics orsurfaces

Inactive ingredients

Water (Aqua), Isopropyl Alcohol,Aloe Barbadensis Leat Juice, Caprylyl Glycol， Glycerin, isopropyl Miristate, Acrylates/C10-30 Alky Acrylate Crosspolymer, Amnomethyl Propanol, Fragrance(parfum)